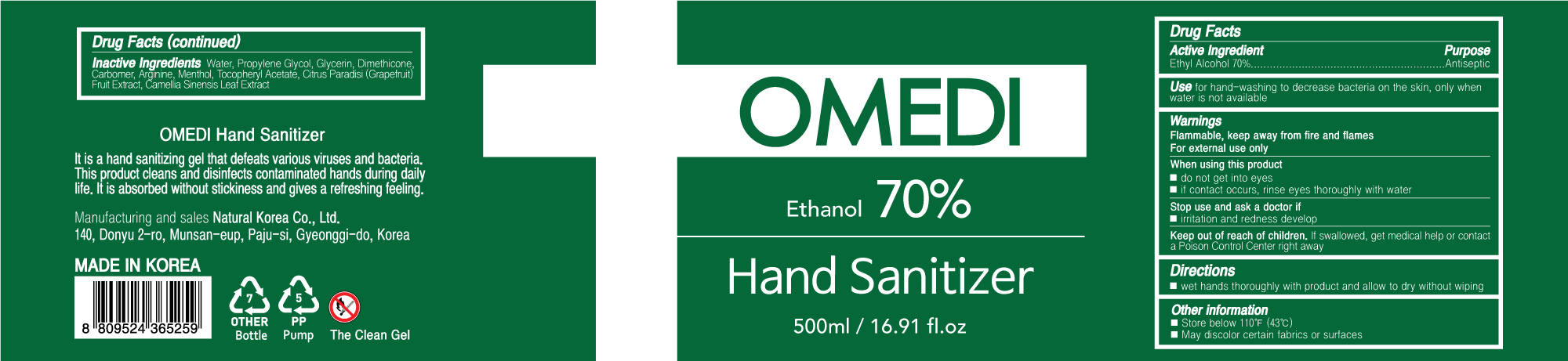 DRUG LABEL: OMEDI HAND SANITIZER
NDC: 74646-0500 | Form: GEL
Manufacturer: Natural Korea Co., Ltd.
Category: otc | Type: HUMAN OTC DRUG LABEL
Date: 20200421

ACTIVE INGREDIENTS: ALCOHOL 350 mL/500 mL
INACTIVE INGREDIENTS: ALPHA-TOCOPHEROL ACETATE; MENTHOL; PROPYLENE GLYCOL; GLYCERIN; DIMETHICONE; GREEN TEA LEAF; WATER; CARBOMER HOMOPOLYMER, UNSPECIFIED TYPE; ARGININE; GRAPEFRUIT

[OMEDI HAND SANITIZER 500 ml : 74646-0500-1